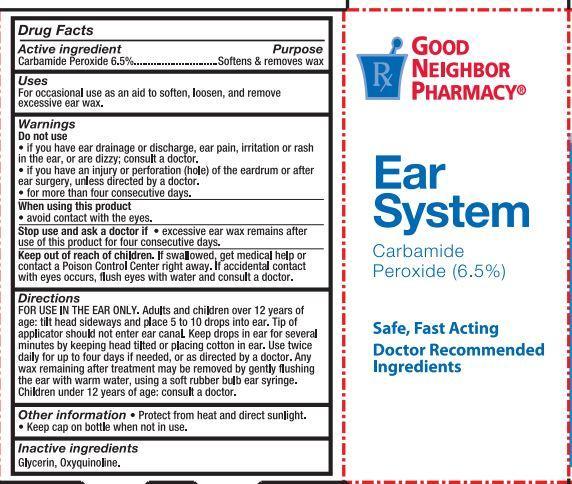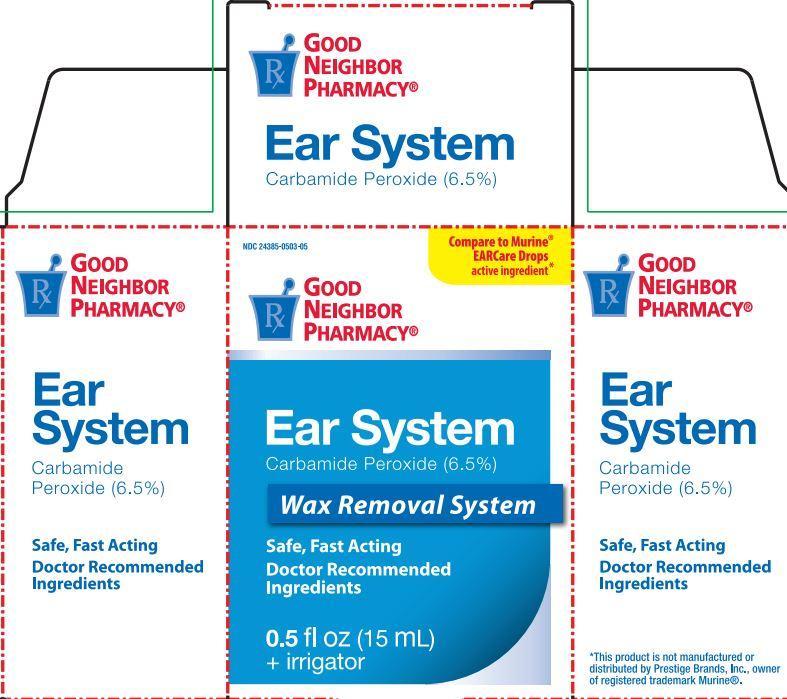 DRUG LABEL: Ear System
NDC: 24385-501 | Form: KIT | Route: TOPICAL
Manufacturer: Amerisource Bergen
Category: otc | Type: HUMAN OTC DRUG LABEL
Date: 20160504

ACTIVE INGREDIENTS: Carbamide Peroxide 6.5 g/100 mL
INACTIVE INGREDIENTS: GLYCERIN; OXYQUINOLINE SULFATE

EarWax Removal Drops
Drug Facts

Active ingredient Purpose

Carbamide Peroxide 6.5% Softens & removes wax

Uses

For occasional use as an aid soften, loosen, and remove excessive ear wax

Warnings

Do not use
• If you have ear drainage or discharge, ear pain, irritation or rash in the ear, or are dizzy; consult a doctor.
• If you have an injury or perforation (hole) of the eardrum or after ear surgery, unless directed by a doctor.
When using this product avoid contact with eyes

Stop use and ask a doctor if excessive earwax remains after use of this product for four consecutive days

Keep out of reach of the children
If product is swallowed, get medical help or contact a Poison Control Center right away
In case of accidental ingestion, seek professional or contact a Poison Control Center immediately.

Directions Directions For use in the ear only.

Adults and children over 12 years of age:
• tilt head sideways and place 5 to 10 drops into ear
• tip of applicator should not enter ear canal
• keep drops in ear for several minutes by keeping head tilted or placing cotton in the ear
• use twice daily for up to 4 days if needed, or as directed by a doctor
• any wax remaining after treatment may be removed by gently flushing the ear with warm water, using a soft rubber bulb ear syringe
Children under 12 years of age: consult a doctor.

Inactive ingredients

Glyceryn, Oxyquinoline